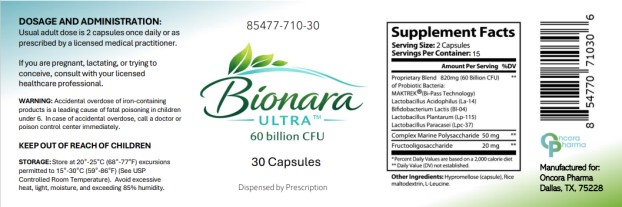 DRUG LABEL: Bionara ULTRA
NDC: 85477-710 | Form: CAPSULE
Manufacturer: Oncora Pharma, LLC
Category: prescription | Type: HUMAN PRESCRIPTION DRUG LABEL
Date: 20260225

ACTIVE INGREDIENTS: LACTOBACILLUS ACIDOPHILUS LA 14 410 mg/1 1; BIFIDOBACTERIUM ANIMALIS LACTIS BL04 410 mg/1 1; LACTIPLANTIBACILLUS PLANTARUM 410 mg/1 1; LACTICASEIBACILLUS PARACASEI LPC-37 410 mg/1 1; LESSONIA NIGRESCENS 25 mg/1 1; BETA VULGARIS ROOT FRUCTOOLIGOSACCHARIDES 10 mg/1 1
INACTIVE INGREDIENTS: HYPROMELLOSE, UNSPECIFIED; MALTODEXTRIN; LEUCINE

Bionara Ultra

PRODUCT DESCRIPTION

Bionara Ultra™ is a prescription probiotic dietary supplement containing a proprietary blend of probiotic bacteria providing 60 billion CFU per serving (2 capsules), combined with prebiotic and polysaccharide support ingredients.

Each serving (2 capsules) contains 820 mg of proprietary probiotic blend delivering 60 billion CFU, including:

- MATREK® (Bi-Pass Technology)
- Lactobacillus acidophilus (La-14)
- Bifidobacterium lactis (Bl-04)
- Lactobacillus plantarum (Lp-115)
- Lactobacillus paracasei (Lpc-37)

INDICATIONS AND USAGE

Bionara Ultra™ is a prescription probiotic supplement intended to support gastrointestinal health and maintain normal intestinal flora balance.

Dispensed by prescription under medical supervision.

DOSAGE AND ADMINISTRATION

Usual adult dose is 2 capsules once or twice daily or as prescribed by a licensed medical practitioner.

WARNINGS

Accidental overdose of iron-containing products is a leading cause of fatal poisoning in children under 6. In case of accidental overdose, call a doctor or poison control center immediately.

If pregnant, lactating, or trying to conceive, consult with a licensed healthcare professional prior to use.

CONTRAINDICATIONS

None known.

STORAGE

Store at 20°–25°C (68°–77°F).
Excursions permitted to 15°–30°C (59°–86°F) [See USP Controlled Room Temperature].

Avoid excessive heat, light, moisture, and exceeding 85% humidity.

HOW SUPPLIED

Bionara Ultra™ is supplied as:

- 30 capsules per bottle
- NDC 85477-710-30

MANUFACTURER INFORMATION

Manufactured for:
Oncora Pharma
Dallas, TX 75228

Principal Display Panel

85477-710-30
Bionara
ULTRA
60 billion CFU
30 Capsules